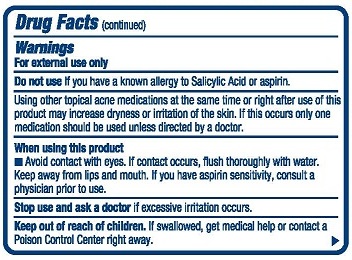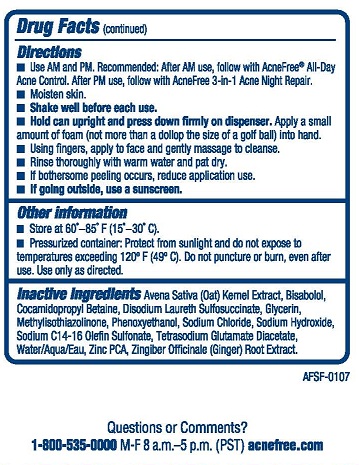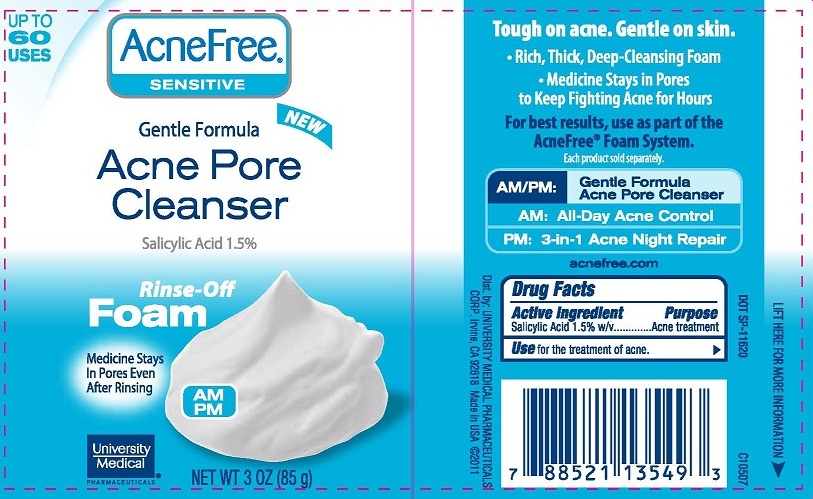 DRUG LABEL: AF Foam Sensitive Acne Pore Cleanser
NDC: 50544-304 | Form: AEROSOL, FOAM
Manufacturer: University Medical Pharmaceuticals Corp
Category: otc | Type: HUMAN OTC DRUG LABEL
Date: 20111214

ACTIVE INGREDIENTS: salicylic acid 1.5 g/100 g
INACTIVE INGREDIENTS: oat; LEVOMENOL; COCAMIDOPROPYL BETAINE; DISODIUM LAURETH SULFOSUCCINATE ; glycerin; METHYLISOTHIAZOLINONE; PHENOXYETHANOL; SODIUM CHLORIDE; SODIUM HYDROXIDE; SODIUM C14-16 OLEFIN SULFONATE ; water; ZINC PIDOLATE; ginger

AF Foam Sensitive Acne Pore Cleanser

Active ingredient: Salicylic Acid 1.5% w/v

Purpose: Acne Treatment

INDICATIONS AND USAGE

Use for the treatment of acne.

Warnings: For external use only

Do not use If you have a known allergy to Salicylic Acid or aspirin.
Using other topical acne medications at the same time or right after use of this product may increase drynes or irritation of the skin. If this occurs only one medication should be used unless directed by a doctor.

When using this product

- Avoid contact with eyes. If contact occurs, flush thoroughly with water. Keep away from lips and mouth. If you have aspirin sensitivity, consult a physician prior to use.

Stop use and ask a doctor if excessive irritation occurs.

Keep out of reach of children. If swallowed, get medical help or contact a Poison Control Center right away.

Directions

- Use AM and PM. Recommended: after AM use, follow with AcneFree All-Day Acne Control. After PM use, follow with AcneFree 3-in-1 Acne Night Repair.
- Moisten skin.
- Shake can before use.
- Press down firmly on dispenser and apply a small amount of foam (not more than a dollop the size of golf ball) into hand.
- Using fingers, apply to face and gently massage to cleanse.
- Rinse thoroughly with warm water and pat dry.
- If bothersome peeling occurs, reduce application use.
- If going outside, use a sunscreen.

Other information

- Store at 60o- 85o F (15o-30o C).
- Pressurized container: Protect from sunlight and do not expose to temperatures exceeding 120oF
  (49o C). Do not puncture or burn, even after use. Use only as directed.

INACTIVE INGREDIENT

Inactive ingredients: Avena Sativa (Oat) Kernel Extract, Bisabolol, Cocamidopropyl Betaine, Disodium Laureth Sulfosuccinate, Glycerin, Methylisothiazolinone, Phenoxyethanol, Sodium Chloride, Sodium Hydroxide, Sodium C14-16 Olefin Sulfonate, Tetrasodium Glutamate Diacetate, Water/Aqua/Eau, Zinc PCA, Zingiber Officinale (Ginger) Root Extact.

PACKAGE LABEL

AcneFree Sensitive
Gentle Formula
Acne Pore Cleanser
Salicylic Acid 1.5%
Rinse-Off Foam
Medicine Stays In Pores Even After Rinsing